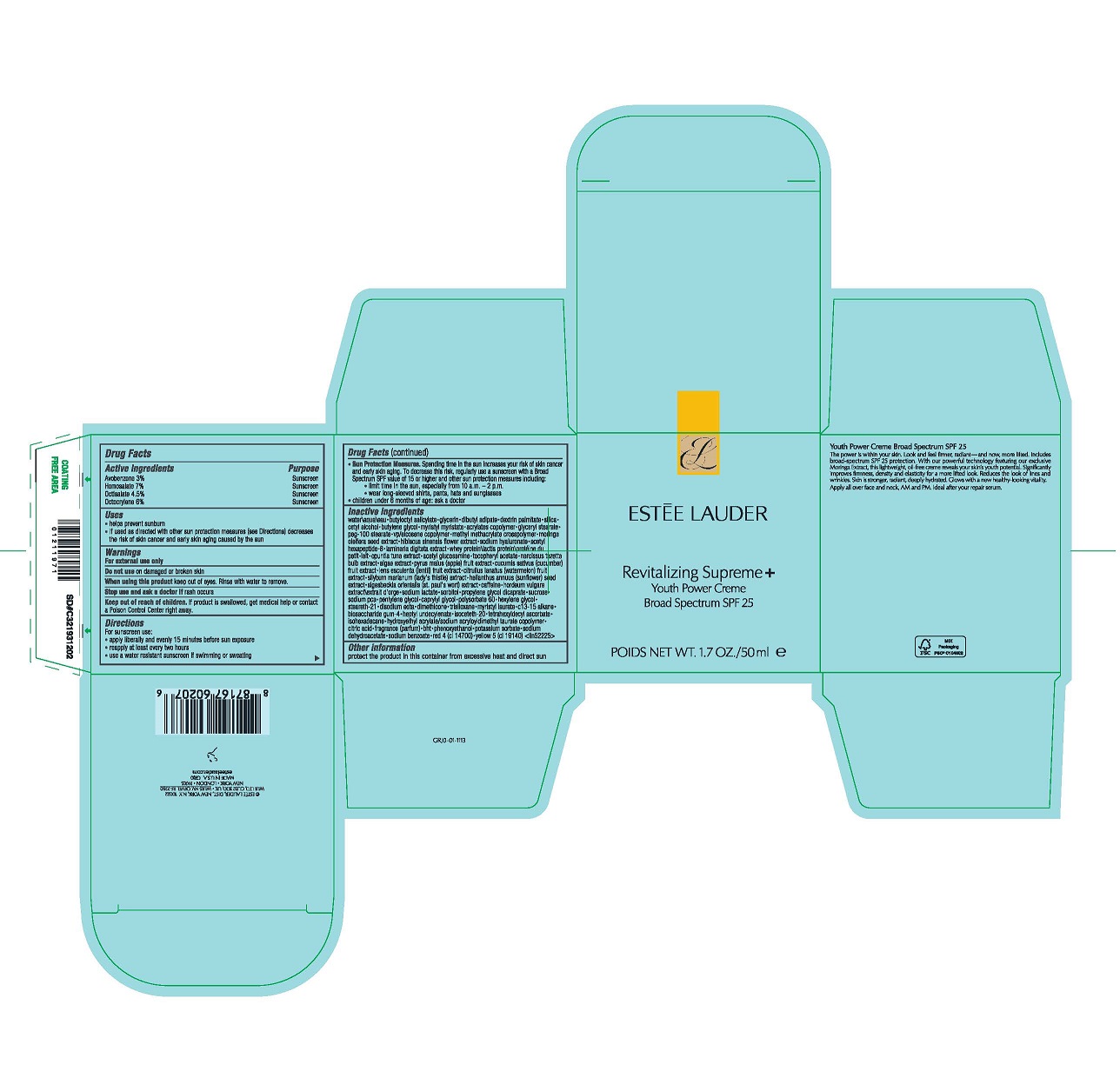 DRUG LABEL: REVITALIZING SUPREME YOUTH POWER Creme BROAD SPECTRUM SPF 25
NDC: 11559-065 | Form: CREAM
Manufacturer: ESTEE LAUDER INC
Category: otc | Type: HUMAN OTC DRUG LABEL
Date: 20240125

ACTIVE INGREDIENTS: AVOBENZONE 30 mg/1 mL; HOMOSALATE 70 mg/1 mL; OCTISALATE 45 mg/1 mL; OCTOCRYLENE 60 mg/1 mL
INACTIVE INGREDIENTS: SUCROSE; TETRAHEXYLDECYL ASCORBATE; CITRIC ACID MONOHYDRATE; CAPRYLYL GLYCOL; BUTYLATED HYDROXYTOLUENE; FD&C YELLOW NO. 5; POLYSORBATE 60; DIMETHICONE; SIGESBECKIA ORIENTALIS FLOWERING TOP; HEPTYL UNDECYLENATE; ISOHEXADECANE; PHENOXYETHANOL; WATERMELON; HORDEUM VULGARE WHOLE; SODIUM PYRROLIDONE CARBOXYLATE; SILYBUM MARIANUM SEED; SUNFLOWER SEED; HYDROXYETHYL ACRYLATE/SODIUM ACRYLOYLDIMETHYL TAURATE COPOLYMER (45000 MPA.S AT 1%); HEXYLENE GLYCOL; STEARETH-21; EDETATE DISODIUM ANHYDROUS; TRISILOXANE; POTASSIUM SORBATE; SODIUM BENZOATE; LENS CULINARIS FRUIT; SORBITOL; C13-15 ALKANE; FD&C RED NO. 4; ISOCETETH-20; SODIUM DEHYDROACETATE; BIOSACCHARIDE GUM-4; HIBISCUS MUTABILIS FLOWER; ALPHA-TOCOPHEROL ACETATE; GLYCERIN; GLYCERYL MONOSTEARATE; ACETYL HEXAPEPTIDE-8; OPUNTIA TUNA FLOWERING TOP; PORPHYRIDIUM PURPUREUM; CUCUMBER; DEXTRIN PALMITATE (CORN; 20000 MW); SILICON DIOXIDE; MYRISTYL MYRISTATE; WHEY; BUTYLENE GLYCOL; LAMINARIA DIGITATA; APPLE; HYALURONATE SODIUM; BUTYLOCTYL SALICYLATE; PEG-100 STEARATE; MORINGA OLEIFERA SEED; METHYL METHACRYLATE/GLYCOL DIMETHACRYLATE CROSSPOLYMER; CAFFEINE; SODIUM LACTATE; PROPYLENE GLYCOL DICAPRATE; PENTYLENE GLYCOL; MYRISTYL LAURATE; DIBUTYL ADIPATE; BUTYL ACRYLATE/METHYL METHACRYLATE/METHACRYLIC ACID COPOLYMER (18000 MW); WATER; CETYL ALCOHOL; VINYLPYRROLIDONE/EICOSENE COPOLYMER; N-ACETYLGLUCOSAMINE; NARCISSUS TAZETTA BULB

REVITALIZING SUPREME+ YOUTH POWER CREME BROAD SPECTRUM SPF 25

Active Ingredients

AVOBENZONE 3%
HOMOSALATE 7%
OCTISALATE 4.5%
OCTOCRYLENE 6%

Purpose

Sunscreen

Uses

- helps prevent sunburn
- if used as directed with other sun protection measures (see Directions) decreases the risk of skin cancer and early skin aging caused by the sun

Warnings

For External Use Only

Do not use

on damaged or broken skin

When using this product

keep out of eyes. Rinse with water to remove.

Stop use

and ask a doctor if rash occurs

Keep out of reach of children.

If product is swallowed, get medical help or contact a Poison Control Center right away.

DOSAGE AND ADMINISTRATION

For sunscreen use:

- apply liberally 15 minutes before sun exposure
- reapply at least every two hours
- use a water resistant sunscreen if swimming or sweating
- Sun Protection Measures. Spending time in the sun increases your risk of skin cancer and early skin aging. To decrease this risk, regularly use a sunscreen with a Broad Spectrum SPF value of 15 or higher and other sun protection measures including:
- limit time in the sun, especially from 10 a.m.–2 p.m.
- wear long-sleeved shirts, pants, hats and sunglasses
- children under 6 months of age: ask a doctor

Inactive Ingredients

WATER\AQUA\EAU,BUTYLOCTYL SALICYLATE,GLYCERIN,DIBUTYL ADIPATE,DEXTRIN PALMITATE,SILICA,CETYL ALCOHOL,BUTYLENE GLYCOL,MYRISTYL MYRISTATE,ACRYLATES COPOLYMER,GLYCERYL STEARATE,PEG-100 STEARATE,VP/EICOSENE COPOLYMER,METHYL METHACRYLATE CROSSPOLYMER,MORINGA OLEIFERA SEED EXTRACT,HIBISCUS SINENSIS FLOWER EXTRACT,SODIUM HYALURONATE,ACETYL HEXAPEPTIDE-8,LAMINARIA DIGITATA EXTRACT,WHEY PROTEIN\LACTIS PROTEIN\PROTÉINE DU PETIT-LAIT,OPUNTIA TUNA EXTRACT,ACETYL GLUCOSAMINE,TOCOPHERYL ACETATE,NARCISSUS TAZETTA BULB EXTRACT,ALGAE EXTRACT,PYRUS MALUS (APPLE) FRUIT EXTRACT,CUCUMIS SATIVUS (CUCUMBER) FRUIT EXTRACT,LENS ESCULENTA (LENTIL) FRUIT EXTRACT,CITRULLUS LANATUS (WATERMELON) FRUIT EXTRACT,SILYBUM MARIANUM (LADY'S THISTLE) EXTRACT,HELIANTHUS ANNUUS (SUNFLOWER) SEED EXTRACT,SIGESBECKIA ORIENTALIS (ST. PAUL'S WORT) EXTRACT,CAFFEINE,HORDEUM VULGARE EXTRACT\EXTRAIT D'ORGE,SODIUM LACTATE,SORBITOL,PROPYLENE GLYCOL DICAPRATE,SUCROSE,SODIUM PCA,PENTYLENE GLYCOL,CAPRYLYL GLYCOL,POLYSORBATE 60,HEXYLENE GLYCOL,STEARETH-21,DISODIUM EDTA,DIMETHICONE,TRISILOXANE,MYRISTYL LAURATE,C13-15 ALKANE,BIOSACCHARIDE GUM-4,HEPTYL UNDECYLENATE,ISOCETETH-20,TETRAHEXYLDECYL ASCORBATE,ISOHEXADECANE,HYDROXYETHYL ACRYLATE/SODIUM ACRYLOYLDIMETHYL TAURATE COPOLYMER,CITRIC ACID,FRAGRANCE (PARFUM),BHT,PHENOXYETHANOL,POTASSIUM SORBATE,SODIUM DEHYDROACETATE,SODIUM BENZOATE,RED 4 (CI 14700),YELLOW 5 (CI 19140) <ILN52225>

Other Information

protect the product in this container from excessive heat and direct sun

PDP

ESTEE LAUDER

Revitalizing Supreme+

Youth Power Creme

Broad Spectrum SPF 25

POIDS NET WT. 1.7OZ/50ml